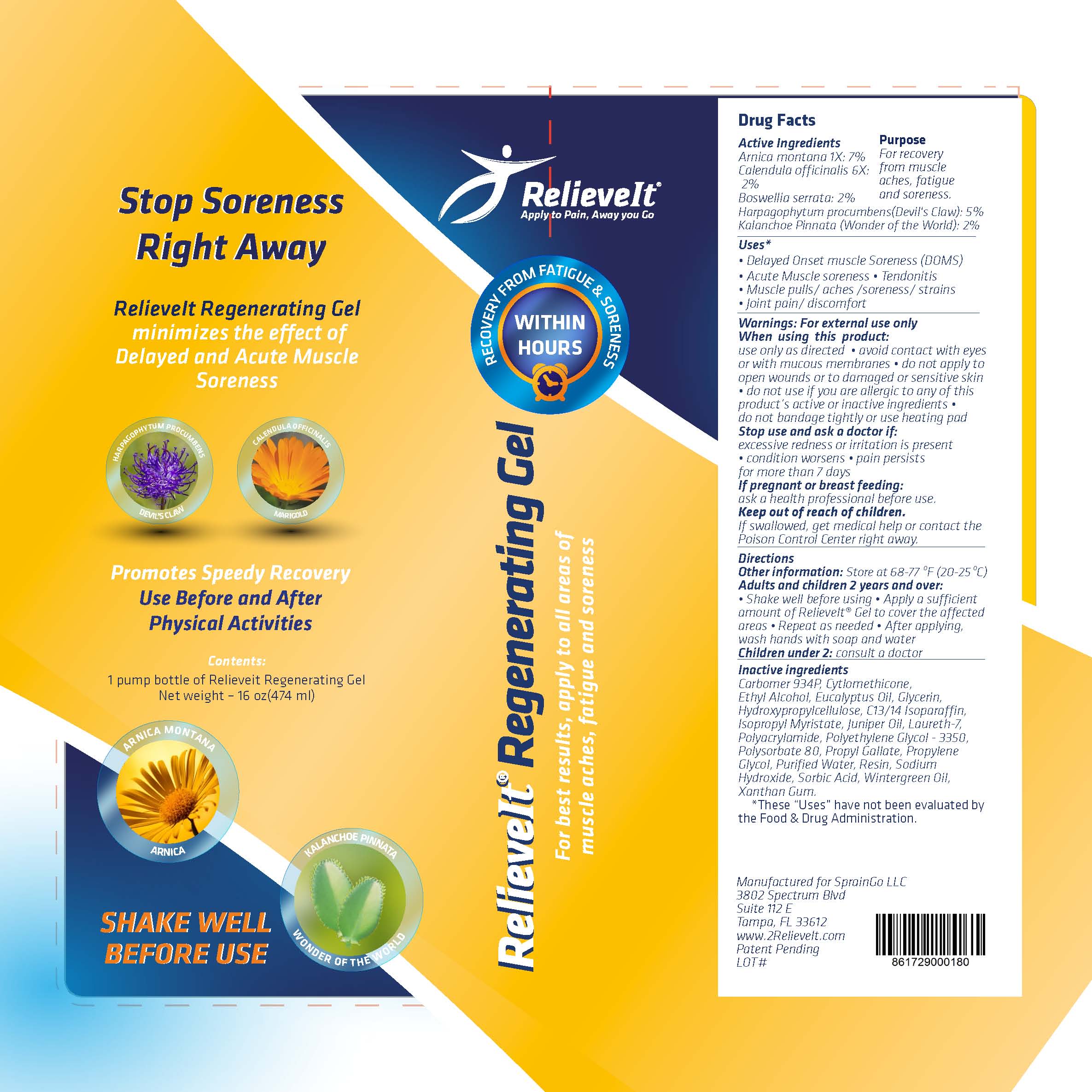 DRUG LABEL: RelieveIt Regenerating Gel
NDC: 58133-952 | Form: GEL
Manufacturer: Cosmetic Specialty Labs, Inc.
Category: homeopathic | Type: HUMAN OTC DRUG LABEL
Date: 20181022

ACTIVE INGREDIENTS: BOSWELLIA SERRATA RESIN OIL 2 [hp_M]/1 mL; ARNICA MONTANA 7 [hp_M]/1 mL; KALANCHOE PINNATA LEAF 2 [hp_M]/1 mL; HARPAGOPHYTUM PROCUMBENS ROOT 5 [hp_M]/1 mL; CALENDULA OFFICINALIS SEED OIL 2 [hp_M]/1 mL
INACTIVE INGREDIENTS: GAULTHERIA PROCUMBENS LEAF; CYCLOMETHICONE; METHYL ALCOHOL; EUCALYPTUS OIL; LOW-SUBSTITUTED HYDROXYPROPYL CELLULOSE, UNSPECIFIED; JUNIPER BERRY OIL; POLYSORBATE 80; BENZOIN RESIN; SODIUM HYDROXIDE; PROPYLENE GLYCOL 2-METHYLBUTYRATE; POLYETHYLENE GLYCOL 3350; PROPYL GALLATE; CARBOMER 934; GLYCERIN; ISOPROPYL MYRISTATE; POLYACRYLAMIDE (10000 MW); SORBIC ACID; XANTHAN GUM; WATER; AMMONIUM LAURETH-7 SULFATE; C13-14 ISOPARAFFIN; SORBITAN MONOOLEATE

RelieveIt Regenerating Gel

Active Ingredient

Arnica montana 1X: 7%

Calendula officinalis 6X: 2%

Boswellia serrata: 2%

Harpagophytum procumbens(Devil's Claw): 5%

Kalanchoe Pinnata (Wonder of the World): 2%

Purpose

For recovery from muscle aches, fatigue and soreness.

Uses:

• Delayed Onset muscle Soreness (DOMS)

• Acute Muscle soreness • Tendonitis

• Muscle pulls/ aches /soreness/ strains

• Joint pain/ discomfort

Warnings:

for external use only

When using this product:

use only as directed • avoid contact with eyes

or mucous membranes • do not apply to open

wounds, damaged, or very sensitive skin • do

not use if you are allergic to any of this product’s

active or inactive ingredients • do not apply

bandage tightly or use heating pad • do not

resume normal activity without the advice of a

- medical professionall

Keep out of reach of children.

If swallowed, get medical help or contact the

Poison Control Center right away.

Directions:

Adults and children 2 years and over:

•Shake well before using •Apply a sufficient

amount of RelieveIt® Regenerating Gel to cover the

affected area • Repeat as needed • After

applying, wash hands with soap and water

Children under 2: consult a doctor

Other ingredients:

Carbomer 934P, Cyclomethicone, Ethyl Alcohol,
Eucalyptus Oil, Glycerin, Hydroxypropyl Cellulose,
C13/14 Isoparaffin, Isopropyl Myristate, Juniper
Oil, Laureth-7, Polyacrylamide, Polyethylene
Glycol 3350, Polysorbate 80, Propyl Gallate,
Propylene Glycol, Purified Water, Resin, Sodium
Hydroxide, Sorbic Acid, Wintergreen Oil,
Xanthan Gum.

*These “Uses” have not been evaluated by the
Food & Drug Administration.

Stop use and ask a doctor if:

excessive redness or irritation is present •

condition worsens • pain persists for more than

7 days

If pregnant or breast feeding:

ask a health professional before use

Other Information

Store at 68-77°F (20-25°C)